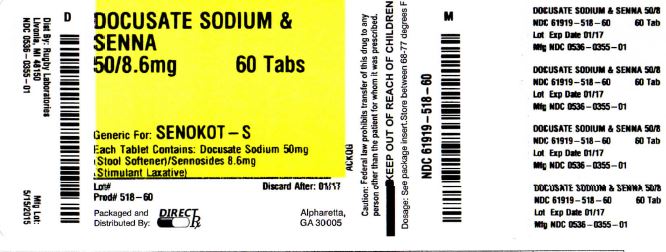 DRUG LABEL: DOCUSATE SODIUM AND SENNA
NDC: 61919-518 | Form: TABLET, FILM COATED
Manufacturer: DIRECT RX
Category: otc | Type: HUMAN OTC DRUG LABEL
Date: 20151109

ACTIVE INGREDIENTS: DOCUSATE SODIUM 50 mg/1 1; SENNOSIDES 8.6 mg/1 1
INACTIVE INGREDIENTS: CARNAUBA WAX; CROSCARMELLOSE SODIUM; DIBASIC CALCIUM PHOSPHATE DIHYDRATE; FD&C BLUE NO. 2; FD&C RED NO. 40; HYPROMELLOSE 2910 (6 MPA.S); HYPROMELLOSE 2910 (15 MPA.S); MAGNESIUM STEARATE; CELLULOSE, MICROCRYSTALLINE; POLYETHYLENE GLYCOL 400; SODIUM BENZOATE; STEARIC ACID; TITANIUM DIOXIDE

DOCUSATE SODIUM AND SENNA

OTC - ACTIVE INGREDIENT SECTION

Active ingredients (in each tablet)
Docusate Sodium 50 mg
Sennosides 8.6 mg

OTC - PURPOSE SECTION

Purposes
Stool Softener
Stimulant Laxative

OTC - KEEP OUT OF REACH OF CHILDREN SECTION

KEEP OUT OF REACH OF CHILDREN SECTION

INDICATIONS & USAGE SECTION

Uses

- relieves occasional constipation
- generally produces bowel movement in 6-12 hours

WARNINGS SECTION

Warnings

OTC - DO NOT USE SECTION

Do not use

- for longer than one week
- if you are taking mineral oil
- when abdominal pain, nausea or vomiting are present

OTC - ASK DOCTOR SECTION

Ask a doctor before use if you have noticed a sudden change in bowel habits that lasts over two weeks

OTC - ASK DOCTOR/PHARMACIST SECTION

Ask a doctor or pharmacist before use if you are taking any other drug. Take this product two or more hours before or after other drugs. Laxatives may affect how other drugs work.

OTC - STOP USE SECTION

Stop use and ask a doctor if

- you have rectal bleeding
- you fail to have a bowel movement after use of this product.

These may indicate a serious condition.

OTC - PREGNANCY OR BREAST FEEDING SECTION

If pregnant or breast-feeding, ask a health professional before use.
Close

DOSAGE & ADMINISTRATION SECTION

Directions
adults and children 12 years and over: 2-4 tablets once daily or in divided doses
children 6 to under 12 years: 1-2 tablets once daily or in divided doses
children 2 to under 6 years: 1/2-1 tablet once daily or in divided doses
children under 2 years: ask a doctor

STORAGE AND HANDLING SECTION

Other information
each tablet contains: calcium 20 mg, sodium 6 mg (LOW SODIUM)
store at 20°-25°C (68°-77°F)

INACTIVE INGREDIENT SECTION

Inactive ingredients carnauba wax, colloidal silicon dioxide, croscarmellose sodium, dibasic calcium phosphate dihydrate, FD-C blue #2 aluminum lake, FD-C red #40 aluminum lake, hypromellose, magnesium stearate, microcrystalline cellulose, polyethylene glycol (PEG), sodium benzoate, stearic acid, titanium dioxide

OTC - QUESTIONS SECTION

Questions or comments?
call 1-800-645-2158, 9 am - 5 pm ET, Monday - Friday